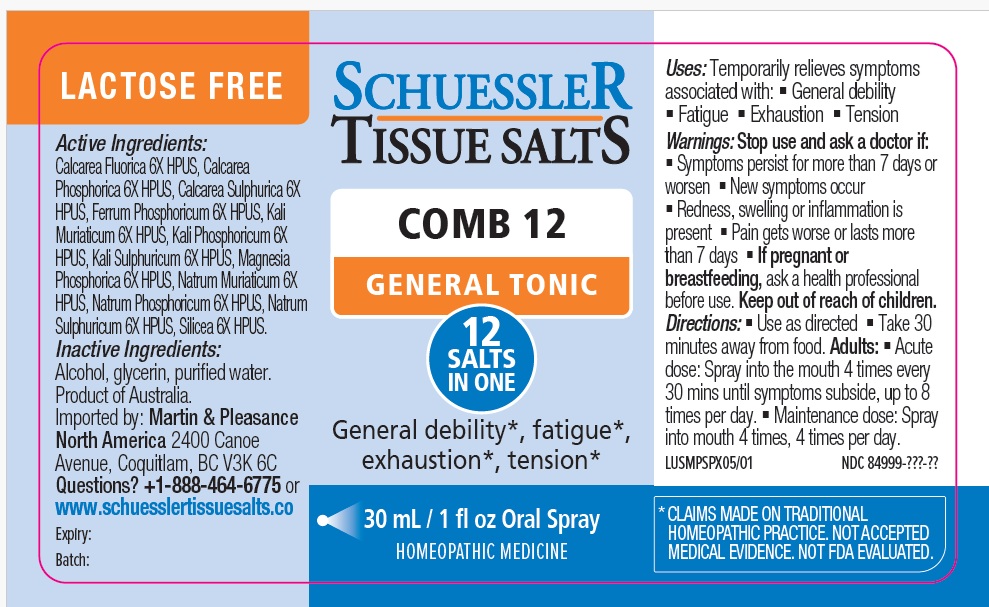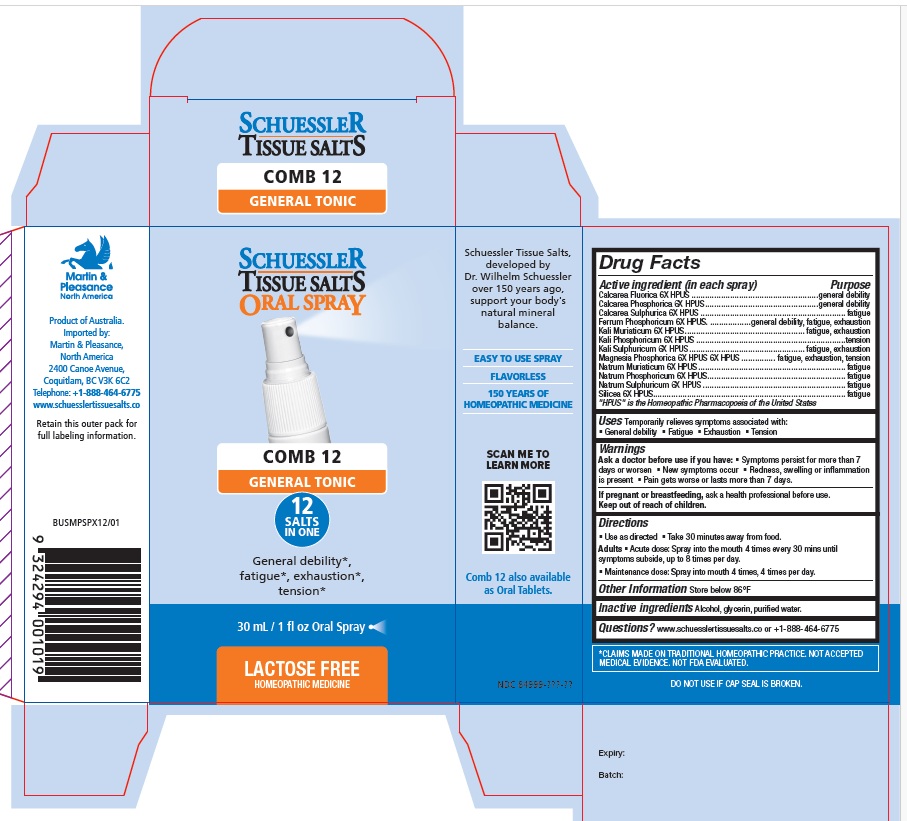 DRUG LABEL: Schuessler Tissue Salts Comb 12 General Tonic
NDC: 84999-030 | Form: SPRAY
Manufacturer: Martin & Pleasance Pty Ltd
Category: homeopathic | Type: HUMAN OTC DRUG LABEL
Date: 20250908

ACTIVE INGREDIENTS: CALCIUM FLUORIDE 6 [hp_X]/30 mL; TRIBASIC CALCIUM PHOSPHATE 6 [hp_X]/30 mL; CALCIUM SULFATE DIHYDRATE 6 [hp_X]/30 mL; FERROUS PHOSPHATE 6 [hp_X]/30 mL; DIBASIC POTASSIUM PHOSPHATE 6 [hp_X]/30 mL; POTASSIUM CHLORIDE 6 [hp_X]/30 mL; MAGNESIUM PHOSPHATE, DIBASIC 6 [hp_X]/30 mL; POTASSIUM SULFATE 6 [hp_X]/30 mL; SODIUM CHLORIDE 6 [hp_X]/30 mL; SODIUM PHOSPHATE, DIBASIC, ANHYDROUS 6 [hp_X]/30 mL; SODIUM SULFATE ANHYDROUS 6 [hp_X]/30 mL; SILICON DIOXIDE 6 [hp_X]/30 mL
INACTIVE INGREDIENTS: ALCOHOL; GLYCERIN; WATER

Active ingredient (in each spray) Purpose

Calcarea Fluorica 6X HPUS ........................................................general debility
Calcarea Phosphorica 6X HPUS..................................................general debility
Calcarea Sulphurica 6X HPUS ................................................................ fatigue
Ferrum Phosphoricum 6X HPUS. ..................general debility, fatigue, exhaustion
Kali Muriaticum 6X HPUS..................................................... fatigue, exhaustion
Kali Phosphoricum 6X HPUS ..................................................................tension
Kali Sulphuricum 6X HPUS................................................... fatigue, exhaustion
Magnesia Phosphorica 6X HPUS ............... fatigue, exhaustion, tension
Natrum Muriaticum 6X HPUS ................................................................. fatigue
Natrum Phosphoricum 6X HPUS............................................................. fatigue
Natrum Sulphuricum 6X HPUS ............................................................... fatigue
Silicea 6X HPUS..................................................................................... fatigue

"HPUS" is the Homeopathic Pharmacopoeia of the United States

Uses

Temporarily relieves symptoms associated with:

- General debility
- Fatigue
- Exhaustion
- Tension

Warnings

Ask a doctor before use if you have:

- Symptoms persist for more than 7 days or worsen
- New symptoms occur
- Redness, swelling, or inflammation is present
- Pain gets worse or lasts more than 7 days.

If you are pregnant or breastfeeding, ask a healthprofessional before use. Keep out of reach of children.

Directions

- Use as directed
- Take 30 minutes away from food.

Adults

- Acute dose: Spray into the mouth 4 times every 30 mins until symptoms subside, up to 8 times per day.
- Maintenance dose: Spray into mouth 4 times, 4 times per day.

Other Information

Store below 86°F

Inactive Ingredients

Alcohol, Glycerin, Purified Water

Questions?www.schuesslertissuesalts.co or + 1-888-464-6775